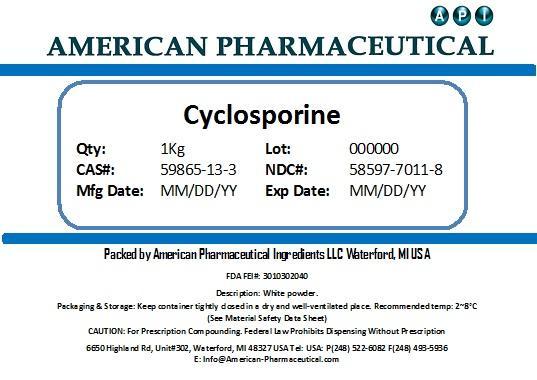 DRUG LABEL: Cyclosporin A
NDC: 58597-7011 | Form: POWDER
Manufacturer: AMERICAN PHARMACEUTICAL INGREDIENTS LLC
Category: other | Type: BULK INGREDIENT
Date: 20131031

ACTIVE INGREDIENTS: CYCLOSPORINE 1 g/1 g

Cyclosporin A